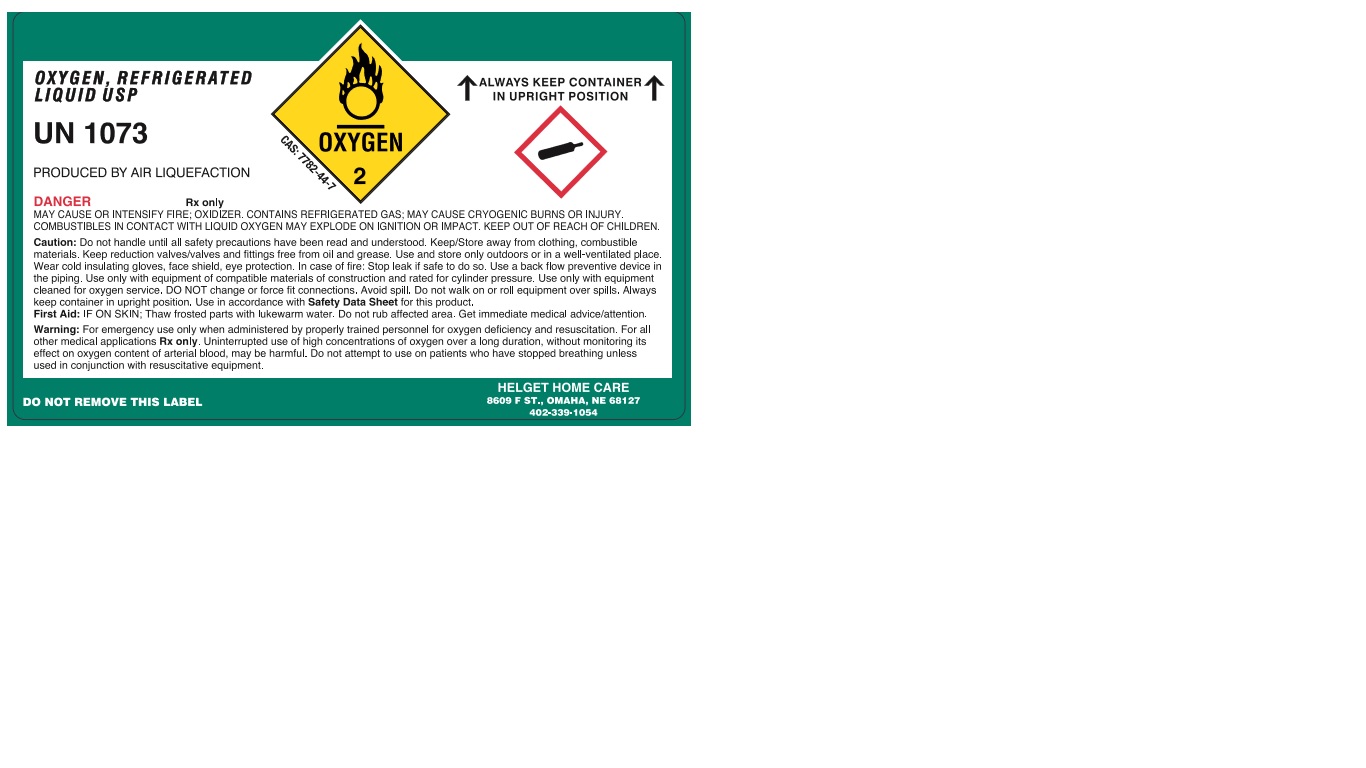 DRUG LABEL: Oxygen
NDC: 26124-002 | Form: GAS
Manufacturer: HELGET, INC.
Category: prescription | Type: HUMAN PRESCRIPTION DRUG LABEL
Date: 20251209

ACTIVE INGREDIENTS: OXYGEN 999 mL/1 L

Oxygen

PACKAGE LABEL

OXYGEN, REFRIGERATED LIQUID USP
UN 1073
CAS: 7782-44-7
PRODUCED BY AIR LIQUEFACTION
ALWAYS KEEP CONTAINER IN UPRIGHT POSITION
DANGER
Rx only
MAY CAUSE OR INTENSIFY FIRE; OXIDIZER. CONTAINS REFRIGERATED GAS; MAY CAUSE CRYOGENIC BURNS OR INJURY. COMBUSTIBLES IN CONTACT WITH LIQUID OXYGEN MAY EXPLODE ON IGNITION OR IMPACT. KEEP OUT OF REACH OF CHILDREN.
Caution: Do not handle until all safety precautions have been read and understood. Keep/Store away from clothing, combustible materials. Keep reduction valves/valves and fittings free from oil and grease. Use and store only outdoors or in a well-ventilated place. Wear cold insulating gloves, face shield, eye protection. In case of fire: Stop leak if safe to do so. Use a back flow preventive device in the piping. Use only with equipment of compatible materials of construction and rated for cylinder pressure. Use only with equipment cleaned for oxygen service. DO NOT change or force fit connections. Avoid spill. Do not walk on or roll equipment over spills. Always keep container in upright position. Use in accordance with Safety Data Sheet for this product.
First Aid: IF ON SKIN; Thaw frosted parts with lukewarm water. Do not rub affected area. Get immediate medical advice/attention.
Warning: For emergency use only when administered by properly trained personnel for oxygen deficiency and resuscitation. For all other medical applications Rx only. Uninterrupted use of high concentrations of oxygen over a long duration, without monitoring its effect on oxygen content of arterial blood, may be harmful. Do not attempt to use on patients who have stopped breathing unless used in conjunction with resuscitative equipment.
DO NOT REMOVE THIS LABEL
HELGET HOME CARE
8609 F ST., OMAHA, NE 68127
402-339-1054